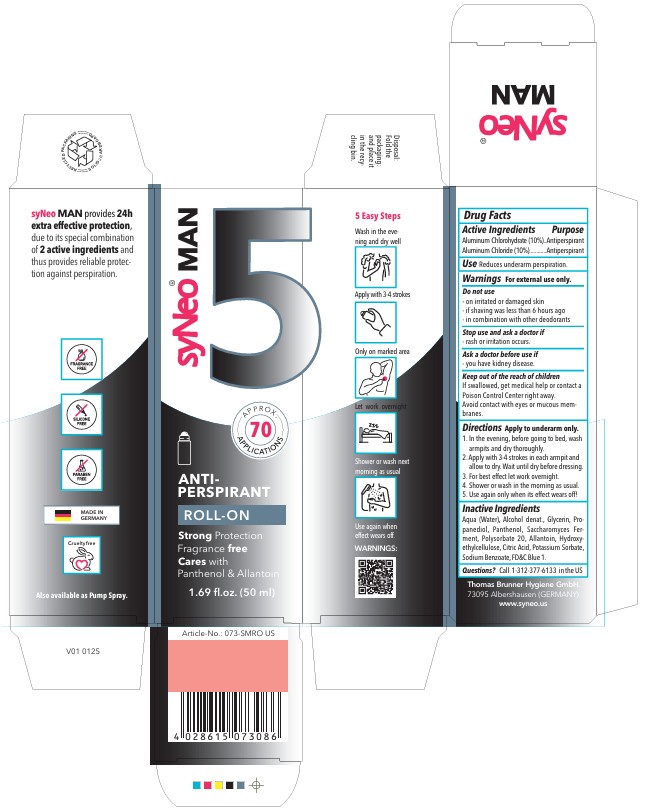 DRUG LABEL: SyNEO MAN ANTI-PERSPIRANT
NDC: 85118-001 | Form: STICK
Manufacturer: Thomas Brunner Hygiene GmbH
Category: otc | Type: HUMAN OTC DRUG LABEL
Date: 20250221

ACTIVE INGREDIENTS: ALUMINUM CHLOROHYDRATE 10 g/100 mL; ALUMINUM CHLORIDE 10 g/100 mL
INACTIVE INGREDIENTS: GLYCERIN; HYDROXYETHYLCELLULOSE; PROPANEDIOL; POLYSORBATE 20; SACCHAROMYCES LYSATE; ALLANTOIN; PANTHENOL; PATENT BLUE V; WATER; ALCOHOL

SyNeo MAN ANTI-PERSPIRANT ROLL-ON

Drug Facts

ACTIVE INGREDIENT

Active Ingredients | Purpose
Aluminum Chlorohydrate (10%) | Antiperspirant
Aluminum Chloride (10%) | Antiperspirant

Use

Reduces underarm perspiration.

Warnings

For external use only.

Stop use and ask a doctor if

- rash or irritation occurs.

Ask a doctor before use if

- you have kidney disease.

Keep out of the reach of children

If swallowed, get medical help or contact a Poison Control Center right away.

Acoid contact with eyes or mucous membranes.

Directions

Apply to underarm only.

1. In the evening, before going to bed, wash armpits and dry thoroughly.
2. Apply with 3-4 strokes in each armpit and allow to dry. Wait until dry before dressing.
3. For best effect let work overnight.
4. Shower or wash in the morning as usual.
5. Use again only when its effect wears off!

Inactive Ingredients

Aqua (Water), Alcohol denat., Glycerin, Propanediol, Panthenol, Saccharomyces Ferment, Polysorbate 20, Allantoin, Hydroxyethylcellulose, Citric Acid, Potassium Sorbate, Sodium Benzoate, FD&C Blue 1.

Questions?

Questions? Call 1-312-377-6133 in the US

SyNEO MAN ANTI-PERSPIRANT ROLL-ON

SyNEO MAN

APPROX 70 APPLICATIONS

ANTI-

PERSPIRANT

ROLL-ON

Strong Protection

Fragrance free

Cares with Panthenol & Allantoin

1.69 fl.oz (50 ml)